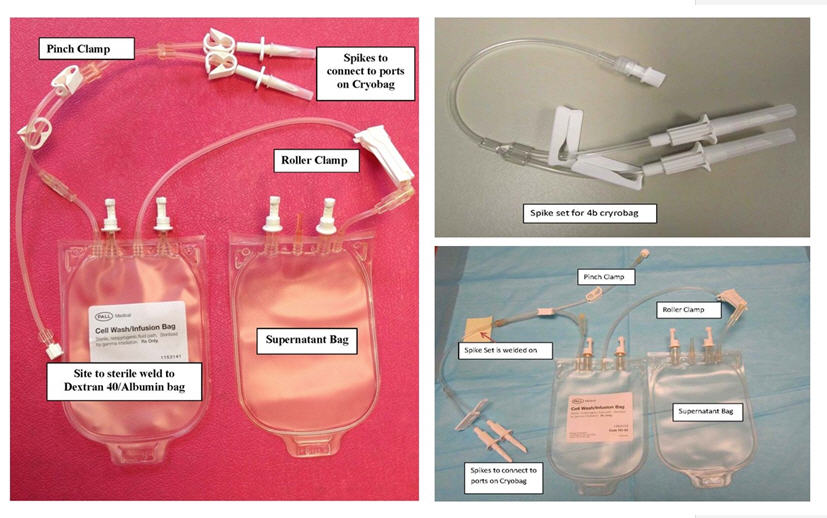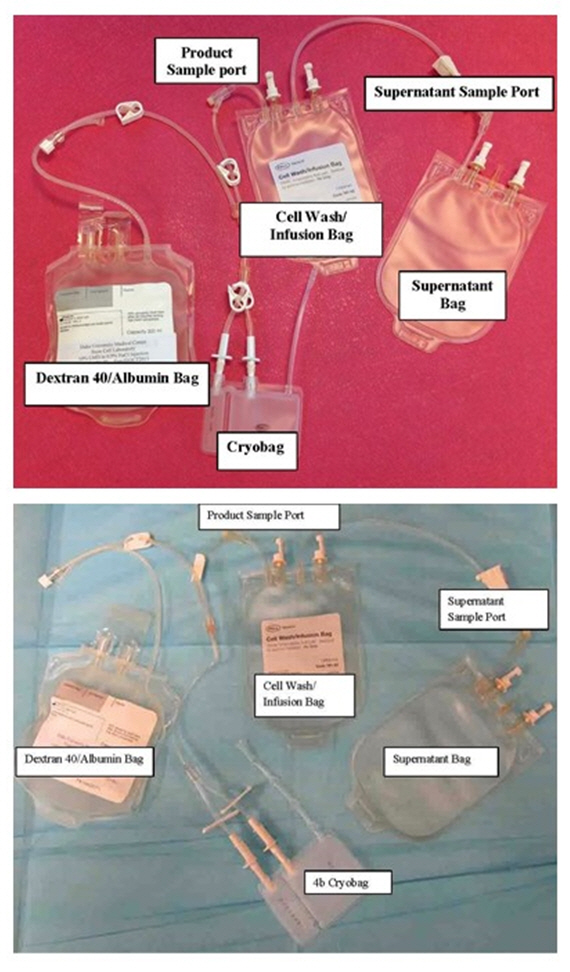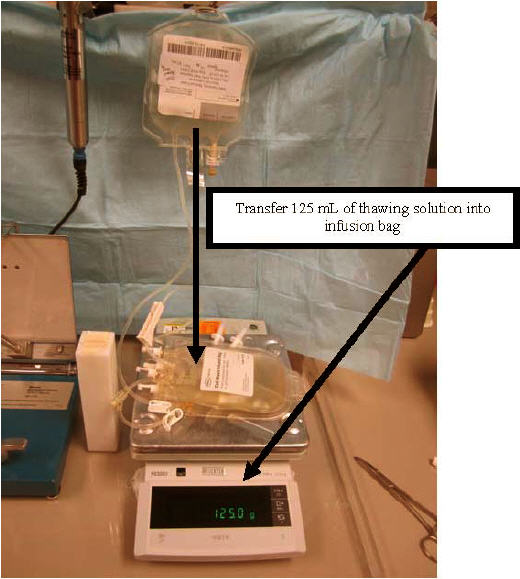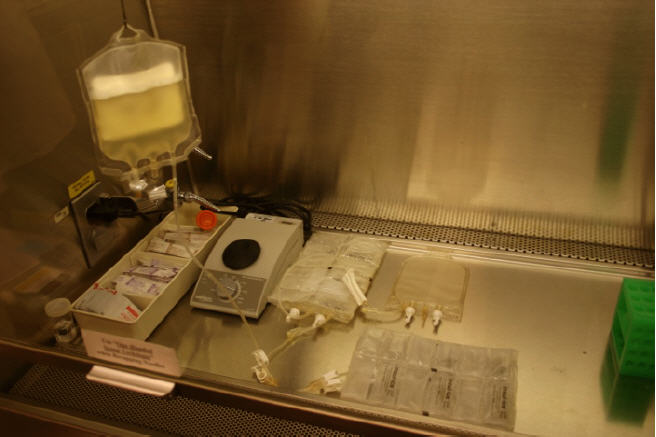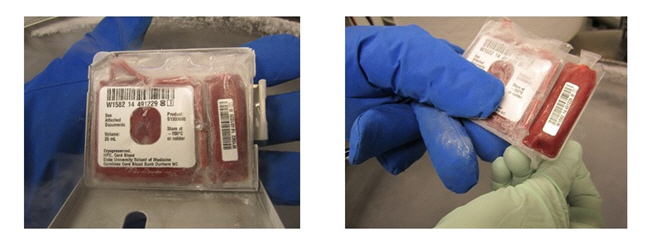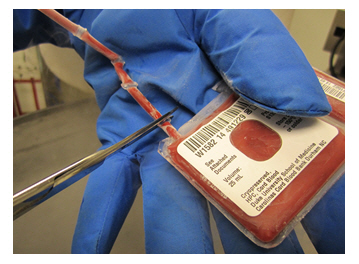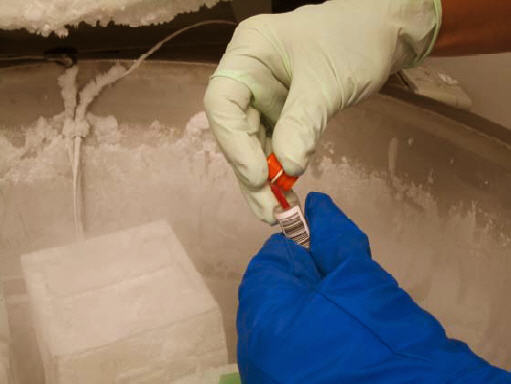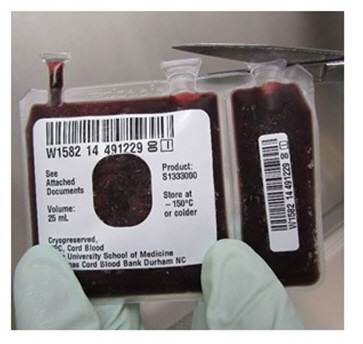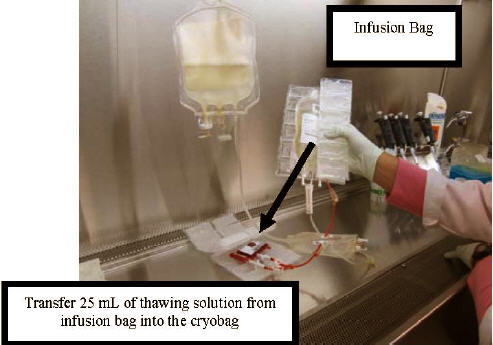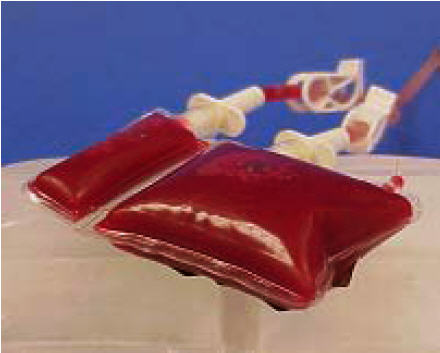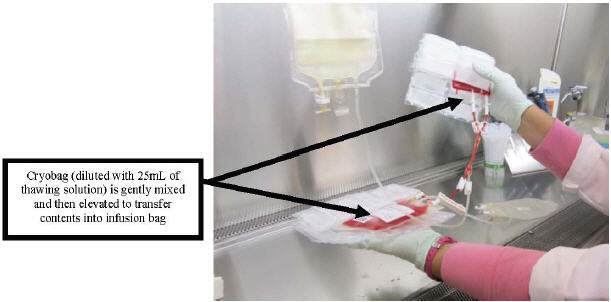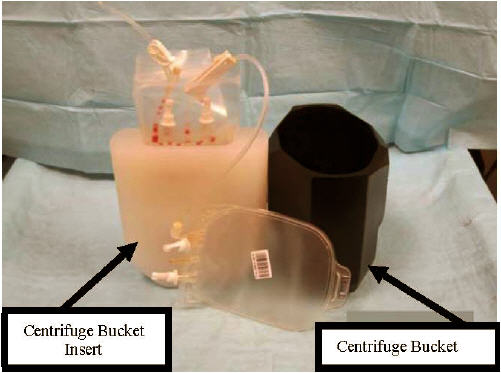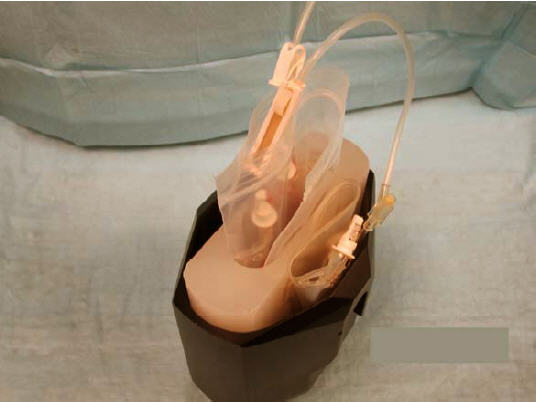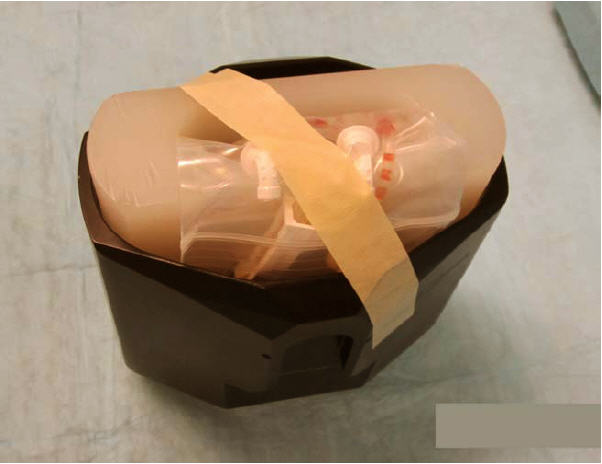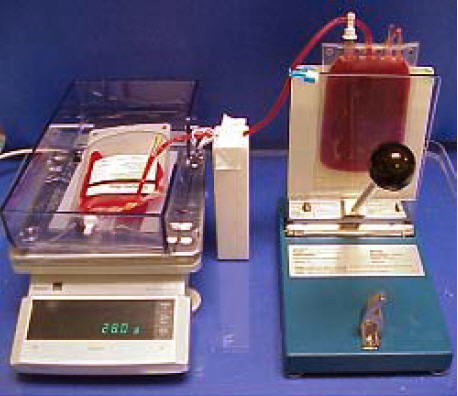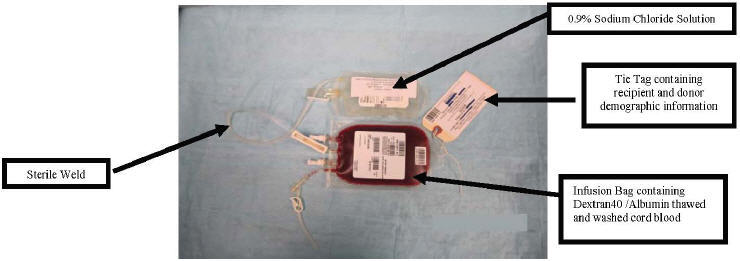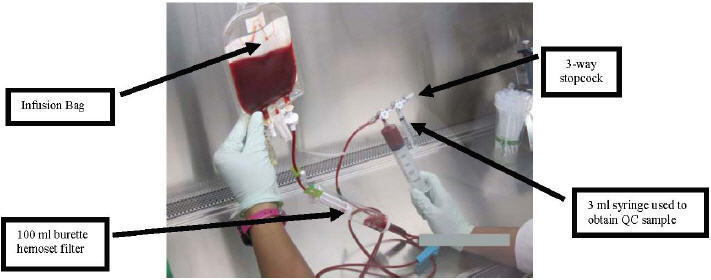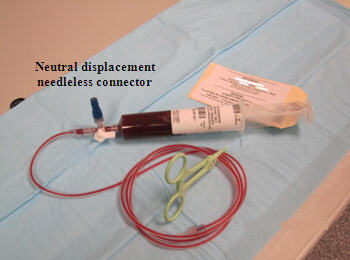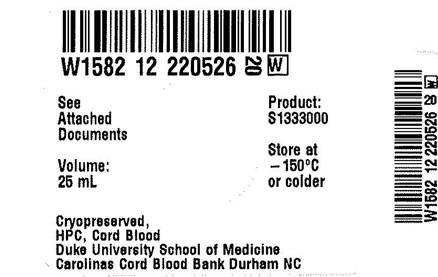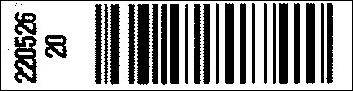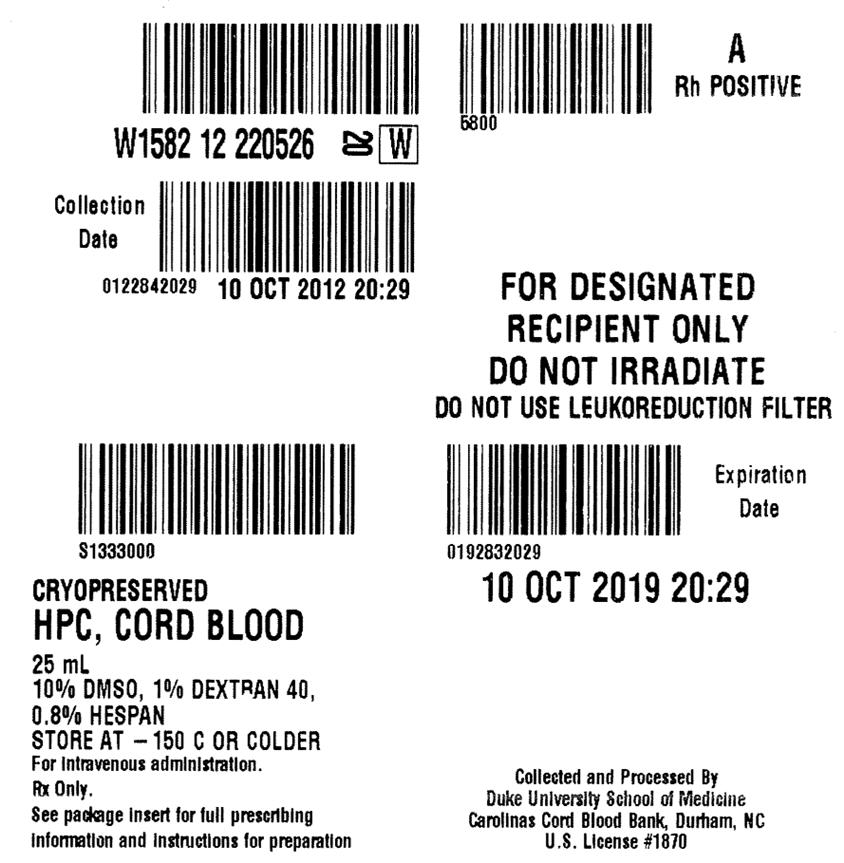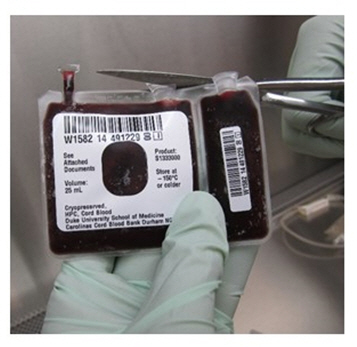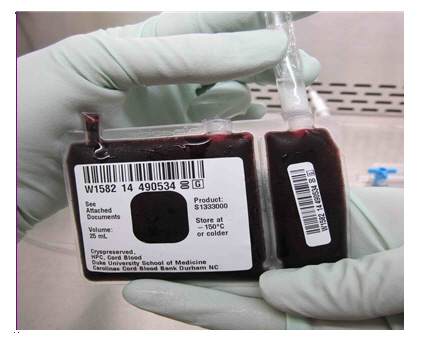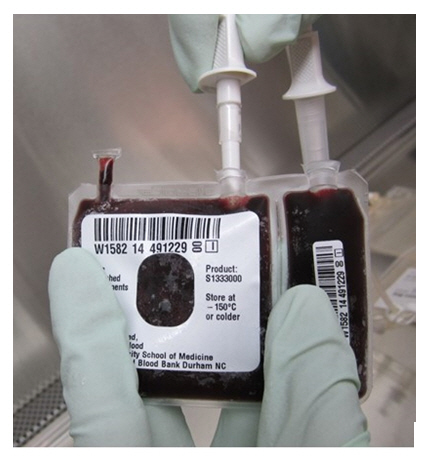 DRUG LABEL: DUCORD
NDC: W1582-S1333 | Form: SOLUTION
Manufacturer: Duke University School of Medicine, Carolinas Cord Blood Bank
Category: other | Type: LICENSED MINIMALLY MANIPULATED CELLS LABEL
Date: 20151104

ACTIVE INGREDIENTS: human cord blood hematopoietic progenitor cell 900000000 1/25 mL
INACTIVE INGREDIENTS: Dimethyl Sulfoxide; Hetastarch; Dextran 40

HIGHLIGHTS OF PRESCRIBING INFORMATION

These highlights do not include all the information needed to use DUCORD safely and effectively. See full prescribing information for DUCORD.
DUCORD (HPC, Cord Blood)
Injectable Suspension for Intravenous Use
Initial U.S. Approval: 2012

WARNING: FATAL INFUSION REACTIONS, GRAFT VERSUS HOST DISEASE, ENGRAFTMENT SYNDROME, AND GRAFT FAILURE

See full prescribing information for complete boxed warning.

- Fatal infusion reactions: Monitor patients during infusion and discontinue for severe reactions. (5.1, 5.2)
- Graft-vs-host disease (GVHD): GVHD may be fatal. Administration of immunosuppressive therapy may decrease the risk of GVHD. (5.3)
- Engraftment syndrome: Engraftment syndrome may be fatal. Treat engraftment syndrome promptly with corticosteroids. (5.4)
- Graft failure: Graft failure may be fatal. Monitor patients for laboratory evidence of hematopoietic recovery. (5.5)

RECENT MAJOR CHANGES

Box Warning | 01/2015
Contraindications (4) | 11/2015

1 INDICATIONS AND USAGE

DUCORD, HPC (Hematopoietic Progenitor Cell), Cord Blood, is an allogeneic cord blood hematopoietic progenitor cell therapy indicated for use in unrelated donor hematopoietic progenitor cell transplantation procedures in conjunction with an appropriate preparative regimen for hematopoietic and immunologic reconstitution in patients with disorders affecting the hematopoietic system that are inherited, acquired, or result from myeloablative treatment. (1)

The risk benefit assessment for an individual patient depends on the patient characteristics, including disease, stage, risk factors, and specific manifestations of the disease, on characteristics of the graft, and on other available treatments or types of hematopoietic progenitor cells. (1)

2 DOSAGE AND ADMINISTRATION

- For intravenous use only.
- Do not irradiate.
- Unit selection and administration of DUCORD should be done under the direction of a physician experienced in hematopoietic progenitor cell transplantation. (2)
- The recommended minimum dose is 2.5 × 10^7 nucleated cells/kg at cryopreservation. (2.1)
- Do not administer DUCORD through the same tubing with other products except for normal saline. (2.3)

3 DOSAGE FORMS AND STRENGTHS

Each unit contains a minimum of 9 × 10^8 total nucleated cells with at least 1.25 × 10^6 viable CD34+ cells at the time of cryopreservation. The exact precryopreservation nucleated cell content of each unit is provided on the container label and accompanying records. (3)

4 CONTRAINDICATIONS

None.

5 WARNINGS AND PRECAUTIONS

- Hypersensitivity Reactions (5.1)
- Infusion Reactions (5.2)
- Graft-versus-Host Disease (5.3)
- Engraftment Syndrome (5.4)
- Graft Failure (5.5)
- Malignancies of Donor Origin (5.6)
- Transmission of Serious Infections (5.7)
- Transmission of Rare Genetic Diseases (5.8)

6 ADVERSE REACTIONS

Mortality, from all causes, at 100 days post-transplant was 25%. (6.1)

The most common infusion-related adverse reactions (≥5%) are hypertension, vomiting, nausea, bradycardia, and fever. (6.1)

To report SUSPECTED ADVERSE REACTIONS, contact the Duke University School of Medicine, Carolinas Cord Blood Bank at 1-919-668- 1102 and FDA at 1-800-FDA-1088 or www.fda.gov/medwatch.

FULL PRESCRIBING INFORMATION

WARNING: FATAL INFUSION REACTIONS, GRAFT VERSUS HOST DISEASE, ENGRAFTMENT SYNDROME, AND GRAFT FAILURE

Fatal infusion reactions: DUCORD administration can result in serious, including fatal, infusion reactions. Monitor patients and discontinue DUCORD infusion for severe reactions. [See Warnings and Precautions (5.1, 5.2)]

Graft-vs-host disease (GVHD): GVHD is expected after administration of DUCORD, and may be fatal. Administration of immunosuppressive therapy may decrease the risk of GVHD. [See Warnings and Precautions (5.3)]

Engraftment syndrome: Engraftment syndrome may progress to multiorgan failure and death. Treat engraftment syndrome promptly with corticosteroids. [See Warnings and Precautions (5.4)]

Graft failure: Graft failure may be fatal. Monitor patients for laboratory evidence of hematopoietic recovery. Prior to choosing a specific unit of DUCORD, consider testing for HLA antibodies to identify patients who are alloimmunized. [See Warnings and Precautions (5.5)]

1 INDICATIONS AND USAGE

DUCORD, HPC (Hematopoietic Progenitor Cell), Cord Blood, is an allogeneic cord blood hematopoietic progenitor cell therapy indicated for use in unrelated donor hematopoietic progenitor stem cell transplantation procedures in conjunction with an appropriate preparative regimen for hematopoietic and immunologic reconstitution in patients with disorders affecting the hematopoietic system that are inherited, acquired, or result from myeloablative treatment.

The risk benefit assessment for an individual patient depends on the patient characteristics, including disease, stage, risk factors, and specific manifestations of the disease, on characteristics of the graft, and on other available treatments or types of hematopoietic progenitor cells.

2 DOSAGE AND ADMINISTRATION

- For intravenous use only.
- Do not irradiate.

Unit selection and administration of DUCORD should be done under the direction of a physician experienced in hematopoietic progenitor cell transplantation.

2.1 Dosing

The recommended minimum dose is 2.5 × 10^7 nucleated cells/kg at cryopreservation. Multiple units may be required in order to achieve the appropriate dose.

Matching for at least 4 of 6 HLA-A antigens, HLA-B antigens, and HLA-DRB1 alleles is recommended. The HLA typing and nucleated cell content for each individual unit of DUCORD are documented on the container label and/or in accompanying records.

2.2 Preparation for Infusion

DUCORD should be prepared by a trained healthcare professional.

- Do not irradiate DUCORD.
- See the appended detailed instructions for preparation of DUCORD for infusion.
- Once prepared for infusion, DUCORD may be stored at 4 to 8 °C for up to 30 minutes if product is thawed and DMSO is not removed, at 4 to 8 °C for up to 1 hour if DUCORD is thawed and diluted to reduce DMSO concentration, and at 4 to 8 °C for up to 4 hours if DMSO is removed in a washing procedure [see Instructions for Preparation for Infusion].
- The recommended limit on DMSO administration is 1 gram per kg body weight per day. [See Warnings and Precautions (5.2) and Overdosage (10 ]

2.3 Administration

DUCORD should be administered under the supervision of a qualified healthcare professional experienced in hematopoietic progenitor cell transplantation.

1. Confirm the identity of the patient for the specified unit of DUCORD prior to administration.
2. Confirm that emergency medications are available for use in the immediate area.
3. Ensure the patient is hydrated adequately.
4. Premedicate the patient 30 to 60 minutes before the administration of DUCORD. Premedication should include any or all of the following: antipyretic, histamine antagonists, and corticosteroids.
5. Inspect the product for any abnormalities, such as unusual particulates, and for breaches of container integrity prior to administration. Prior to infusion, discuss all such product irregularities with the laboratory issuing the product for infusion.
6. Administer DUCORD by intravenous infusion. Do not administer in the same tubing concurrently with products other than 0.9% Sodium Chloride, Injection (USP). DUCORD may be filtered through a 170 to 260 micron filter designed to remove clots. Do NOT use a filter designed to remove leukocytes.
7. DUCORD should be infused over 15 to 60 minutes depending on the volume of the product and the weight of the patient. The rate of infusion should not exceed a maximum of 5 milliliters per kilogram per hour. The infusion rate should be reduced if the fluid load is not tolerated. The infusion should be discontinued in the event of an allergic reaction or if the patient develops a moderate to severe infusion reaction. [See Warnings and Precautions (5.2) and Adverse Reactions (6)]
8. Monitor the patient for adverse reactions during, and for at least six hours after, administration. Because DUCORD contains lysed red cells that may cause renal failure, careful monitoring of urine output is also recommended.

NOTE: If product is being prepared for a multi-unit infusion, infuse units independently.

Should a reaction occur, appropriately manage the reaction before the second unit is thawed for infusion.

3 DOSAGE FORMS AND STRENGTHS

Each unit of DUCORD contains a minimum of 9.0 × 10^8 total nucleated cells with a minimum of 1.25 × 10^6 viable CD34+ cells, suspended in 10% dimethyl sulfoxide (DMSO) and 1% Dextran 40, at the time of cryopreservation.

The exact pre-cryopreservation nucleated cell content is provided on the container label and in accompanying records.

4 CONTRAINDICATIONS

None.

5 WARNINGS AND PRECAUTIONS

5.1 Hypersensitivity Reactions

Allergic reactions may occur with infusion of HPC, Cord Blood, including DUCORD. Reactions include bronchospasm, wheezing, angioedema, pruritus, and hives [see Adverse Reactions (6)]. Serious hypersensitivity reactions, including anaphylaxis, also have been reported. These reactions may be due to dimethyl sulfoxide (DMSO), Dextran 40, hydroxyethylstarch, or a plasma component of DUCORD.

DUCORD may contain residual antibiotics if the cord blood donor was exposed to antibiotics in utero. Patients with a history of allergic reactions to antibiotics should be monitored for allergic reactions following DUCORD administration.

5.2 Infusion Reactions

Infusion reactions are expected to occur and include nausea, vomiting, fever, rigors or chills, flushing, dyspnea, hypoxemia, chest tightness, hypertension, tachycardia, bradycardia, dysgeusia, hematuria, and mild headache. Premedication with antipyretic, histamine antagonists, and corticosteroids may reduce the incidence and intensity of infusion reactions.

Severe reactions, including respiratory distress, severe bronchospasm, severe bradycardia with heart block or other arrhythmias, cardiac arrest, hypotension, hemolysis, elevated liver enzymes, renal compromise, encephalopathy, loss of consciousness, and seizure also may occur. Many of these reactions are related to the amount of DMSO administered. Minimizing the amount of DMSO administered may reduce the risk of such reactions, although idiosyncratic responses may occur even at DMSO doses thought to be tolerated. The actual amount of DMSO depends on the method of preparation of the product for infusion. Limiting the amount of DMSO infused to no more than 1 gram per kilogram per day is recommended. [See Overdosage (10)]

Infusion reactions may begin within minutes of the start of infusion of DUCORD, although symptoms may continue to intensify and not peak for several hours after completion of the infusion. Monitor the patient closely during this period. When a reaction occurs, discontinue the infusion and institute supportive care as needed.

If infusing more than one unit of DUCORD on the same day, do not administer subsequent units until all signs and symptoms of infusion reactions from the prior unit have resolved.

5.3 Graft-versus-Host Disease

Acute and chronic graft-versus-host disease (GVHD) may occur in patients who have received DUCORD. Classic acute GVHD is manifested as fever, rash, elevated bilirubin and liver enzymes, and diarrhea. Patients transplanted with DUCORD also should receive immunosuppressive drugs to decrease the risk of GVHD. [See Adverse Reactions (6.1)]

5.4 Engraftment Syndrome

Engraftment syndrome is manifested as unexplained fever and rash in the peri-engraftment period. Patients with engraftment syndrome also may have unexplained weight gain, hypoxemia, and pulmonary infiltrates in the absence of fluid overload or cardiac disease. If untreated, engraftment syndrome may progress to multiorgan failure and death. Once engraftment syndrome is recognized, begin treatment with corticosteroids to ameliorate the symptoms. [See Adverse Reactions (6.1)]

5.5 Graft Failure

Primary graft failure, which may be fatal, is defined as failure to achieve an absolute neutrophil count greater than 500 per microliter blood by Day 42 after transplantation. Immunologic rejection is the primary cause of graft failure. Patients should be monitored for laboratory evidence of hematopoietic recovery. Consider testing for HLA antibodies in order to identify patients who are alloimmunized prior to transplantation and to assist with choosing a unit with a suitable HLA type for the individual patient. [See Adverse Reactions (6.1)]

5.6 Malignancies of Donor Origin

Patients who have undergone HPC, Cord Blood transplantation may develop post-transplant lymphoproliferative disorder (PTLD), manifested as a lymphoma-like disease favoring nonnodal sites. PTLD is usually fatal if not treated.

The incidence of PTLD appears to be higher in patients who have received antithymocyte globulin. The etiology is thought to be donor lymphoid cells transformed by Epstein-Barr virus (EBV). Serial monitoring of blood for EBV DNA may be warranted in high-risk groups.

Leukemia of donor origin also has been reported in HPC, Cord Blood recipients. The natural history is presumed to be the same as that for de novo leukemia.

5.7 Transmission of Serious Infections

Transmission of infectious disease may occur because DUCORD is derived from human blood. Disease may be caused by known or unknown infectious agents. Donors are screened for increased risk of infection with human immunodeficiency virus (HIV), human T-cell lymphotropic virus (HTLV), hepatitis B virus (HBV), hepatitis C virus (HCV), T. pallidum, T. cruzi, West Nile Virus (WNV), transmissible spongiform encephalopathy (TSE) agents, and vaccinia. Donors are also screened for clinical evidence of sepsis, and communicable disease risks associated with xenotransplantation. Maternal blood samples are tested for HIV types 1 and 2, HTLV types I and II, HBV, HCV, T. pallidum, WNV, and T. cruzi. DUCORD is tested for sterility. There may be an effect on the reliability of the sterility test results if the cord blood donor was treated with antibiotics. These measures do not totally eliminate the risk of 6 of 30 transmitting these or other transmissible infectious diseases and disease agents. Report the occurrence of a transmitted infection to Duke University School of Medicine, Carolinas Cord Blood Bank at 1-919-668-1102.

Testing is also performed for evidence of donor infection due to cytomegalovirus (CMV).

Test results may be found in accompanying records.

5.8 Transmission of Rare Genetic Diseases

DUCORD may transmit rare genetic diseases involving the hematopoietic system for which donor screening and/or testing has not been performed [see Adverse Reactions (6.1)]. Cord blood donors have been screened by family history to exclude inherited disorders of the blood and marrow. DUCORD has been tested to exclude donors with sickle cell anemia, and anemias due to abnormalities in hemoglobins C, D, and E. Because of the age of the donor at the time DUCORD collection takes place, the ability to exclude rare genetic diseases is severely limited.

6 ADVERSE REACTIONS

Day-100 mortality from all causes was 25%.

The most common infusion-related adverse reactions (≥5%) are hypertension, vomiting, nausea, bradycardia, and fever.

6.1 Clinical Trials Experience

Because clinical trials are conducted under widely varying conditions, adverse reaction rates observed in the clinical trials of a drug cannot be directly compared to rates in the clinical trials of another drug and may not reflect the rates observed in practice.

The safety assessment of DUCORD is based primarily on review of the data submitted to the FDA dockets from various sources, the dataset for the COBLT Study, and published literature.

Infusion Reactions

The data described in Table 1 reflect exposure to 442 infusions of HPC, Cord Blood (from multiple cord blood banks) in patients treated using a total nucleated cell dose ≥2.5 × 10^7/kg on a single-arm trial or expanded access use (The COBLT Study). The population was 60% male and the median age was 5 years (range 0.05-68 years), and included patients treated for hematologic malignancies, inherited metabolic disorders, primary immunodeficiencies, and bone marrow failure. Preparative regimens and graft-vs-host disease prophylaxis were not standardized. The most common infusion reactions were hypertension, vomiting, nausea, and sinus bradycardia. Hypertension and any grades 3-4 infusion-related reactions occurred more frequently in patients receiving HPC, Cord Blood in volumes greater than 150 milliliters and in pediatric patients. The rate of serious adverse cardiopulmonary reactions was 0.8%.

Table 1. Incidence of Infusion-Related Adverse Reactions Occurring in ≥1% of Infusions (The COBLT Study)
 | Any grade | Grade 3-4
Any reaction | 65.4% | 27.6%
Hypertension | 48.0% | 21.3%
Vomiting | 14.5% | 0.2%
Nausea | 12.7% | 5.7%
Sinus bradycardia | 10.4% | 0
Fever | 5.2% | 0.2%
Sinus tachycardia | 4.5% | 0.2%
Allergy | 3.4% | 0.2%
Hypotension | 2.5% | 0
Hemoglobinuria | 2.1% | 0
Hypoxia | 2.0% | 2.0%

Information on infusion reactions was available from voluntary reports for 388 infusions for patients who received DUCORD at a total nucleated cell dose of ≥2.5×10^7/kg. The population included 57% males and 43% females with median age of 16 years (range 0.1-79 years). Preparative regimens and graft-vs-host disease prophylaxis were not standardized. The reactions were not graded. Nineteen percent of infusions (n=72) were associated with an infusion reaction. The most common infusion reactions, occurring in >1% of infusions, were hypertension (15%), nausea or vomiting (3.4%), bradycardia (1.8%), and chest pain (1.3%).

Other Adverse Reactions

For other adverse reactions, the raw clinical data from the docket were pooled for 1299 (120 adult and 1179 pediatric) patients transplanted with HPC, Cord Blood (from multiple cord blood banks) with total nucleated cell dose ≥2.5 × 10^7/kg. Of these, 66% (n=862) underwent transplantation as treatment for hematologic malignancy. The preparative regimens and graft-vshost disease prophylaxis varied. The median total nucleated cell dose was 6.4 × 10^7/kg (range, 2.5-73.8 10^7/kg). For these patients, Day-100 mortality from all causes was 25%. Primary graft failure occurred in 16%; 42% developed grades 2-4 acute graft-vs-host disease; and 19% developed grades 3-4 acute graft-vs-host disease.

Data from published literature and from observational registries, institutional databases, and cord blood bank reviews reported to the docket for HPC, Cord Blood (from multiple cord blood banks) revealed nine cases of donor cell leukemia, one case of transmission of infection, and one report of transplantation from a donor with an inheritable genetic disorder. The data are not sufficient to support reliable estimates of the incidences of these events.

In the COBLT Study, 15% of the patients developed engraftmentsyndrome.

8 USE IN SPECIFIC POPULATIONS

8.1 Pregnancy

Risk Summary

There are no data with DUCORD use in pregnant women to inform a product-associated risk. Animal reproduction studies have not been conducted with DUCORD. In the U.S. general population, the estimated background risk of major birth defects and miscarriage in clinically recognized pregnancies is 2-4% and 15-20%, respectively.

8.2 Lactation

Risk Summary

There is no information regarding the presence of DUCORD in human milk, the effects on the breastfed infant, or the effects on milk production. The developmental and health benefits of breastfeeding should be considered along with the mother's clinical need for DUCORD and any potential adverse effects on the breastfed infant from DUCORD or from the underlying maternal condition.

8.4 Pediatric Use

HPC, Cord Blood has been used in pediatric patients with disorders affecting the hematopoietic system that are inherited, acquired, or resulted from myeloablative treatment. [See Dosage and Administration (2), Adverse Reactions (6), and Clinical Studies (14)]

8.5 Geriatric Use

Clinical studies of HPC, Cord Blood (from multiple cord blood banks) did not include sufficient numbers of subjects aged 65 and over to determine whether they respond differently than younger subjects. In general, administration of DUCORD to patients over age 65 should be cautious, reflecting their greater frequency of decreased hepatic, renal, or cardiac function, and of concomitant disease or other drug therapy.

8.6 Renal Disease

DUCORD contains Dextran 40 which is eliminated by the kidneys. The safety of DUCORD has not been established in patients with renal insufficiency or renal failure.

10 OVERDOSAGE

10.1 Human Overdosage Experience

There has been no experience with overdosage of HPC, Cord Blood in human clinical trials. Single doses of DUCORD up to 9.1 × 10^8 TNC/kg have been administered. HPC, Cord Blood prepared for infusion may contain dimethyl sulfoxide (DMSO). The maximum tolerated dose of DMSO has not been established, but it is customary not to exceed a DMSO dose of 1 gm/kg/day when given intravenously. Several cases of altered mental status and coma have been reported with higher doses of DMSO.

10.2 Management of Overdose

For DMSO overdosage, general supportive care is indicated. The role of other interventions to treat DMSO overdosage has not been established.

11 DESCRIPTION

DUCORD consists of hematopoietic progenitor cells, monocytes, lymphocytes, and granulocytes from human cord blood for intravenous infusion. Blood recovered from umbilical cord and placenta is volume reduced and partially depleted of red blood cells and plasma.

The active ingredient is hematopoietic progenitor cells which express the cell surface marker CD34. The potency of cord blood is determined by measuring the numbers of total nucleated cells (TNC) and CD34+ cells, and cell viability. Each unit of DUCORD contains a minimum of 9 × 10^8 total nucleated cells with at least 1.25 × 10^6 viable CD34+ cells at the time of cryopreservation. The cellular composition of DUCORD depends on the composition of cells in the blood recovered from the umbilical cord and placenta of the donor. The actual nucleated cell count, the CD34^+ cell count, the ABO group, and the HLA typing are listed on the container label and/or accompanying records sent with each individual unit.

DUCORD has the following inactive ingredients: dimethyl sulfoxide (DMSO), citrate phosphate dextrose (CPD), hydroxyethylstarch, and Dextran 40. When prepared for infusion according to instructions, the infusate contains the following inactive ingredients: Dextran 40, human serum albumin, residual DMSO, and CPD.

12 CLINICAL PHARMACOLOGY

12.1 Mechanism of Action

Hematopoietic stem/progenitor cells from HPC, Cord Blood migrate to the bone marrow where they divide and mature. The mature cells are released into the bloodstream, where some circulate and others migrate to tissue sites, partially or fully restoring blood counts and function, including immune function, of blood-borne cells of marrow origin. [See Clinical Studies (14)]

In patients with enzymatic abnormalities due to certain severe types of storage disorders, mature leukocytes resulting from HPC, Cord Blood transplantation may synthesize enzymes that may be able to circulate and improve cellular functions of some native tissues. However, the precise mechanism of action is unknown.

14 CLINICAL STUDIES

The effectiveness of DUCORD, as defined by hematopoietic reconstitution, was demonstrated in one single-arm prospective study, and in retrospective reviews of data from an observational database for DUCORD and data in the dockets and public information. Of the 1299 patients in the dockets and public data, 66% (n=862) underwent transplantation as treatment for hematologic malignancy. Results for patients who received a total nucleated cell dose ≥2.5 × 10^7/kg are shown in Table 2. Neutrophil recovery is defined as the time from transplantation to an absolute neutrophil count more than 500 per microliter. Platelet recovery is the time to a platelet count more than 20,000 per microliter. Erythrocyte recovery is the time to a reticulocyte count greater than 30,000 per microliter. The total nucleated cell dose and degree of HLA match were inversely associated with the time to neutrophil recovery in the docket data.

Table 2. Hematopoietic Recovery for Patients Transplanted with HPC, Cord Blood Total Nucleated Cell (TNC) Dose ≥2.5 × 10^7/kg
Data Source | The COBLT Study [HPC, Cord Blood (from multiple cord blood banks)] | Docket and Public Data | DUCORD
Design | Single-arm prospective | Retrospective | Retrospective
Number of patients | 324 | 1299 | 550
Median age (range) | 4.6 (0.07 – 52.2) yrs | 7.0 (<1 – 65.7) yrs | 11 (0.083 – 79) yrs
Gender | 59% male 41% female | 57% male 43% female | 56% male 44% female
Median TNC Dose (range) (× 10^7/kg) | 6.7 (2.6 – 38.8) | 6.4 (2.5 – 73.8) | 6.6 (2.5 – 58)
Neutrophil Recovery at Day 42 (95% CI) | 76% (71% – 81%) | 77% (75% – 79%) | 95% [The analysis of hematopoietic recovery is based on a different number of patients, ranging from 402-535, for each variable.] (92% – 96%)
Platelet Recovery at Day 100 (20,000/uL) (95% CI) | 57% (51% – 63%) | - | 92% (89% – 96%)
Platelet Recovery at Day 100 (50,000/uL) (95% CI) | 46% (39% – 51%) | 45% (42% – 48%) | 71% (66% – 75%)
Erythrocyte Recovery at Day 100 (95% CI) | 65% (58% – 71%) | - | -
Median time to Neutrophil Recovery | 27 days | 25 days | 21 days
Median time to Platelet Recovery (20,000/uL) | 90 days | - | 46 days
Median time to Platelet Recovery (50,000/uL) | 113 days | 122 days | 61 days
Median time to Erythrocyte Recovery | 64 days | - | -

16 HOW SUPPLIED/STORAGE AND HANDLING

DUCORD is supplied as a cryopreserved cell suspension in a sealed bag containing a minimum of 9 × 10^8 total nucleated cells with a minimum of 1.25 × 10^6 viable CD34+ cells in a volume of 25 milliliters (ISBT 128, Product Code S1333000, ISBT 128 Facility Identifier Number W1582). The exact pre-cryopreservation nucleated cell content is provided on the container label and accompanying records.

DUCORD units manufactured prior to 01-06-2014 are supplied in a cryopreservation bag with up to 3 attached segments and spike ports that are compatible with the Pall Cell wash/infusion bag set (see section I in Instructions for Preparation for Infusion below). DUCORD units manufactured on and after 01-06-2014 are supplied in the Biosafe 4b bag, which contains up to 4 attached segments and slightly modified spike ports. The 4b bag must be spiked with the Biosafe 4b coupler, which can be heat-sealed to the Pall Cell wash/infusion bag set (see section II,3 in Instructions for Preparation for Infusion below). The year of manufacture is noted in the ISBT number (W1582 14…, for manufacture in 2014), and the specific date of manufacture can be found on page 3 of the NMDP CBU Detail Report.

STORAGE AND HANDLING

Store DUCORD at or below -150 °C until ready for thawing and preparation.

17 PATIENT COUNSELING INFORMATION

Discuss the following with patients receiving DUCORD:

- Report immediately any signs and symptoms of acute infusion reactions, such as fever, chills, fatigue, breathing problems, dizziness, nausea, vomiting, headache, or muscle aches.
- Report immediately any signs or symptoms suggestive of graft-vs-host disease, including rash, diarrhea, or yellowing of the eyes.

INSTRUCTIONS FOR PREPARATION FOR INFUSION

I MATERIALS AND EQUIPMENT
  1 Materials
    - Albumin (human) 25%, USP
    - Dextran 40 in Sodium Chloride Injection, USP (10% Low Molecular Weight Dextran in 0.9% Sodium Chloride Injection)
    - 0.4% Trypan Blue vital stain solution
    - 0.9% Sodium Chloride Injection, USP (normal saline solution)
    - Cell wash/infusion bag set (Pall Medical Cell Wash/Infusion Bag Set or equivalent)
    - Coupler spike set (Biosafe for 4b cryobag) for CBUs manufactured on or after 01-06-2014.
    - 150 and 300 mL transfer bags
    - Sampling site coupler
    - 3, 20, 30 and 60 mL sterile disposable syringes
    - 16 gauge injection needles
    - Alcohol cleaned scissors
    - 5 mL sterile culture tubes (snap cap)
    - 5 mL polystyrene tubes
    - 2 mL Cryogenic vials (Nunc or equivalent)
    - Alcohol prep pads and/or isopropyl alcohol
    - Iodine swab sticks
    - 7 × 8 inch sterile zip-lock bags (or similar size)
    - Hemostats (optional)
    - Tape
    - Gloves
    - Protective freezer gloves
    - Reusable ice mats (Insul-Ice Mat or equivalent)
    - 4 × 4 inch sterile gauze pads (or similar size)
    - 250 mL blood bank centrifuge insert (or similar size)
    - 100 mL burette hemoset 170-260 micron filter
    - 2-gang, 3-way stopcocks with male-luer-lock (or equivalent)
    - Lipid compatible 3-way stopcock
    - Rubber-shod clamp
    - 60 inch, 2.4 mL extension set tubing (APV or equivalent)
    - Neutral displacement needleless connector (ICU Medical MicroCLAVE EndCap or equivalent)
    - 4 – 5 inch sterile spinal needle or other sterilized blunt needle-like device with luer-lock tip
    - Product labels (ISBT [International Society of Blood Transfusion] or equivalent)
    - Forms:
      - Site specific forms generated to capture processing data and to accompany the infusion product to the bedside
      - Cord Blood Unit (CBU) Shipment Packing Information Form: to acknowledges Product ID and shipping information. This form is retained at the transplant center
      - National Marrow Donor Program (NMDP) Receipt of Cord Blood Unit Form: completed by transplant center and return to Duke University School of Medicine, Carolinas Cord Blood Bank (CCBB)
  2 Equipment
    - Biological Safety Cabinet
    - Refrigerated blood bank centrifuge (Sorvall or equivalent)
    - Buckets and supports (inserts) to centrifuge blood bags in the refrigerated blood bank centrifuge
    - Plasma extractor or expressor
    - Scale (with Plexiglass tray or equivalent)
    - Sterile tubing welder device
    - Tube heat sealer for polyvinyl chloride (PVC) plastic
    - Automated cell counter
    - Optical microscope
    - Vortex mixer
    - Water bath (4 liters or more at 37°C)
    - Thermogenesis canister opener
    - Non frost-free refrigerator
    - Transport container (validated to maintain temperature between 4-8°C)
    - Tube rack
    - Vapor phase liquid nitrogen (LN2) freezer
II PREPARATION
  1 General Preparation Information
    a. Use aseptic technique in a biological safety cabinet for all processing steps, including all open-container processing and all spiking of blood bag ports.
    b. Use only sterile materials when processing the cellular product.
    c. Record the manufacturer information, lot number and expiration date (if applicable) of all reagents and disposables.
    d. For CBUs manufactured on or after 01-06-2014 in the Biosafe 4b cryobag, replace spike ports to cryobag with Biosafe 4b coupler kit (included in shipment) per steps in Section II.3 below.
    e. Pre-cool Dextran 40 solution to 4-8°C in refrigerator before mixing with human albumin to prepare the thawing solution.
    f. Verify the water bath is full and that the temperature is 37°C.
    g. Verify the centrifuge is set at 2-8ºC.
    h. Keep thawed product at 2-8ºC throughout the procedure.
    i. Schedule the infusion time of the transplant with the transplant team in advance of the procedure. Re-confirm on the day of infusion with the transplant team so that the start time for the thawing procedure can be adjusted to have the unit ready for infusion at a time the patient can receive the infusion.
    j. Confirm the final product volume required for infusion (based on the patient's weight or not more than 60 mL for the Syringe Method) with the transplant team prior to thawing DUCORD. Record on appropriate laboratory form.
    k. Read section VIII EMERGENCY PRODUCT RECOVERY IN THE EVENT OF A CONTAINER FAILURE prior to thawing product. Always thaw and centrifuge the cryobag and or infusion bag inside of a sterile zip-lock bag so that the product can be recovered if leakage occurs. If the product leaks from the cryobag into the sterile zip-lock bag, use the product recovery process described below in section VIII.
    l. Contact the CCBB Laboratory Supervisor at 919-257-9273 or 919-668-2066 if during thawing, any portion of the product or container appears to be damaged or compromised. The CCBB will provide advice to determine the best way to recovery the product from the compromised container. The CCBB will also provide further instructions for return of the container, if requested, and a prompt investigation will follow. The transplant physician and the local laboratory director should also be notified immediately.
  2 Prepare Dextran 40/Albumin Solution (Thawing Solution)
    a. Use sterile technique to connect an empty 300 mL transfer bag to a 500 mL bag of Dextran 40 solution.
    b. Place the empty transfer bag on the scale and tare the scale.
    c. Transfer 150 grams of pre-cooled Dextran 40 solution to the 300 mL transfer bag.
    d. Heat seal tubing and detach Dextran 40 solution bag from the 300 mL transfer bag by cutting tubing at the sealed point leaving sufficient tubing length for sterile welding later. (See step 3b below)
    e. Insert a sampling site coupler into one of the ports of the 300 mL transfer bag containing the Dextran 40 solution.
    f. Clean the rubber stopper of human albumin bottle with alcohol wipes.
    g. Use a 30 mL syringe to draw up 30 mL of 25% human albumin.
    h. Clean coupler port with alcohol and inject 30 mL of human albumin into the transfer bag containing 150 mL of Dextran 40 solution.
      NOTE: The transfer bag now contains a total of approximately 180 mL of solution containing both Dextran 40 and human albumin and will be referred to as the Dextran 40/Albumin bag in subsequent steps. The solution in this bag (with the final concentration of 8.3% Dextran 40/4.2 % Albumin) will be referred to as the thawing solution.
  3 Assemble the Closed System
    a. Clamp all tubing and place assigned labels on the cell wash/infusion bag set (cell/wash infusion bag attached to supernatant bag) (see Figure 1).
      NOTE: The cell wash/infusion bag will be referred to as infusion bag in subsequent steps.
      Figure 1 –Cell Wash/Infusion Set (left), Spike Set for 4b Bag Only (top right) and Cell Wash/Infusion Set for 4b bag (bottom right)
    b. Sterile weld the cell wash/infusion set to the Dextran 40/Albumin bag (see configuration in Figure 2).
      Figure 2 – Bag Configuration (top with Pall bag and bottom with 4b bag)
    c. For units in the Biosafe 4b bag, heat seal twice and remove the spikes to the cryobag on the Pall cell/wash kit. Sterile weld the spike couplers for the 4b kit.
    d. Place the infusion bag on the scale.
    e. Tare scale and transfer 125 grams (125 mL) of thawing solution from the Dextran 40/Albumin bag into the infusion bag (see Figure 3).
      Figure 3
    f. Clamp off tubing between the Dextran 40/Albumin bag and the infusion bag, using pinch clamp provided with the set.
    g. Wrap the infusion bag with an ice mat.
    h. Place the cell/wash infusion set joined to the Dextran 40/Albumin bag containing thawing solution inside the hood (see Figure 4).
    i. Elevate and hang the Dextran 40/Albumin bag to facilitate flow (see Figure 4).
  4 Assemble Materials and Equipment in Hood
    Figure 4
    a. Assemble all materials needed in the biological safety cabinet before thawing DUCORD (see Figure 4).
    b. Leave one ice mat ready for the cryobag after thawing (see Figure 4).
    c. Assemble site specific forms and apply barcode labels to forms.
    d. Prepare and label all sample tubes for quality control (QC) and sterility testing with patient information, unit number, date and product type.
    e. Place supplies needed for the procedure inside the biological safety cabinet:
      - tube rack
      - 2-mL cryogenic vials
      - test tubes (5 mL polystyrene tubes, 5 mL sterile culture tubes with snap cap)
      - syringes
      - iodine and alcohol swabs
      - sterile gauze pads
      - disinfected scissors
      - sampling site coupler
      - ice mats
      - vortex
III DUCORD THAWING
  1 Preparation for Thawing
    a. Work in the vapor phase of the LN2 freezer.
    b. Remove DUCORD from metal cassette.
    c. Confirm the ISBT barcodes on DUCORD cryobag with a second technologist or designee.
      - Barcodes on DUCORD cryobag should match the labels on the metal cassette, the tie tag and on the accompanying paperwork.
      - Document label check by both individuals.
    d. Remove overwrap plastic sealant (see Figure 5a).
      Figure 5a
    e. Visually inspect the cryobag for damage or cracks.
    f. Cut the cryobag segments, if present (see Figure 5b).
      Figure 5b
    g. Place the segments in a labeled 2 mL cryogenic vial (see Figure 5c) and return to LN2 freezer. Segments may be stored in the liquid or vapor phase of liquid nitrogen as long as the temperature is maintained at less than -150°C.
      Figure 5c
  2 Thawing Procedure
    a. Gently wipe the outside surface of the cryobag with alcohol.
    b. Place the cryobag inside a 7 × 8 inch sterile zip-lock bag, let out the air, and seal the zip-lock bag.
    c. Confirm and document, with a second technologist or designee, that the label on DUCORD cells to be transplanted matches the label on the metal cassette, the tie tag and accompanying paperwork.
    d. Thaw the unit in a 37°C water bath until the product reaches a slushy/liquid consistency. This generally takes about 1-2 minutes.
    e. Treat the thawed cell suspension very gently. The cell membranes are fragile and the cells are lysed easily.
    f. Dry the outside of the ziplock bag containing the slushy cryobag and wipe with alcohol before placing in the biological safety cabinet.
IV DUCORD DILUTION
  1 Preparation for Dilution
    a. Remove the thawed cryobag from zip-lock bag.
    b. Clean outside of the port covers with iodine swab sticks.
    c. Remove both port covers with alcohol cleaned scissors (Figure 6a and 6b).
      Figure 6a
      Figure 6b
    d. Clean cut surfaces, first with iodine, and then with alcohol (see Figure 6c).
      Figure 6c
    e. Dry the cut surfaces with sterile gauze.
    f. Insert the spikes (see Figure 6d) on the infusion bag (see Figure 1) in the dry and disinfected ports on the cryobag one at the time (see Figure 2).
      Figure 6d
    g. Wrap the cryobag with an ice mat.
    h. Unclamp tubing between infusion bag and cryobag.
  2 Dilution of DUCORD
    a. Slowly transfer over approximately 1-2 minutes 25 mL of chilled (4-8°C) thawing solution from the infusion bag into the cryobag (see Figure 7a) until both compartments of the cryobag bulge (see Figure 7b).
      NOTE: It is important to add the thawing solution slowly over 1-2 minutes so that the dimethyl sulfoxide (DMSO) in the product is gradually diluted.
      Figure 7a
      Figure 7b
    b. Gently mix by hand the incoming thawing solution and slushy product during transfer.
    c. Gently rock the cryobag by hand for 1-3 minutes for complete homogenization of its contents.
    d. Elevate the cryobag to gradually transfer the diluted cell suspension from the cryobag into the infusion bag which is wrapped in an ice mat to keep the product cool at 4-8°C.
      NOTE: At this point in the procedure, the infusion bag contains 50 mL of material from the cryobag (25 mL product + 25 mL thawing solution) mixed with the remaining 100 mL of thawing solution in the infusion bag for a total of approximately 150 mL.
    e. Mix the fluids during transfer by moving the bags up and down (see Figure 8).
      Figure 8
    f. Leave the remaining residual fluid and cells in the cryobag at this time.
    g. Gently rock the infusion bag by hand for 1-2 minutes to allow complete mixing.
    h. Clamp the lines between the cryobag and the infusion bag in preparation for the rinsing process.
  3 First Rinse of the Cryobag
    a. Unclamp tubing between the Dextran 40/Albumin bag and the cryobag.
    b. Add approximately 25 mL of thawing solution from the Dextran 40/Albumin bag to both compartments of the cryobag.
      NOTE: A total of 150 mL of thawing solution has been used to mix with the product at the completion of this step.
    c. Clamp tubing between the Dextran 40/Albumin bag and the cryobag after transfer.
    d. Apply gentle pressure and massage the cryobag to dislodge all remaining cells.
    e. Swirl the thawing solution around the inside of the cryobag to resuspend and harvest all remaining cells.
    f. Open clamp between the cryobag and the infusion bag.
    g. Elevate the cryobag to allow the thawing solution and cells to flow into the infusion bag.
    h. Gently mix the fluids during transfer by rocking the infusion bag by hand.
    i. Compress and roll the cryobag to remove all the remaining cell suspension.
    j. Drain all the solution from the cryobag into the infusion bag.
    k. Clamp off the line from the infusion bag in preparation for the second rinse of the cryobag.
  4 Second Rinse of the Cryobag
    a. Again, unclamp the tubing between the Dextran 40/Albumin bag and the empty cryobag.
    b. Add approximately 25 mL of thawing solution from the Dextran 40/Albumin bag to both compartments of the empty cryobag.
      NOTE: A total of 175 mL of thawing solution has been used to mix with the product at the completion of this step.
    c. Repeat steps c to j of the First Rinse of the Cryobag procedure above.
    d. Drain any remaining thawing solution from the Dextran 40/Albumin bag into the infusion bag.
      NOTE: At this point in the procedure, the product and thawing solution are mixed together in the infusion bag for a total volume of approximately 200-205 mL.
    e. Heat seal tubing between the infusion bag and the cryobag, then detach the cryobag by cutting at the sealed point.
    f. Remove the unit identifying label from the cryobag, place it on the paperwork and discard the empty cryobag.
    g. Heat seal tubing between the infusion bag and the Dextran 40/Albumin bag, then detach the infusion bag by cutting at the sealed point.
      NOTES: The volume of the diluted product should be close to 200 mL. A volume higher than 225 mL may cause bag breakage.
    h. If the product is going to be administered in the diluted state (e.g. without further washing):
      - Label the infusion bag with patient and donor information per institutional standard operation procedures (Demand 128 or equivalent).
      - Attach a tie tag containing the recipient and donor demographic information to the infusion bag.
      - Take a 0.9 mL sample for quality control testing (see section VII).
      - Transport diluted product to the site of administration to the patient in a validated transport container at 4-8°C.
      - Infuse within one hour of thawing.
      - Infuse the product through a 100 mL burette hemoset 170-260 micron filter.
        Do not use leukoreduction filters.
V DUCORD WASH
  1 Centrifugation of Thawed/Diluted Product
    a. Check that the centrifuge is set at 2-8°C.
    b. At this point, the infusion bag remains attached, by tubing, to the supernatant bag.
    c. Place the infusion bag inside a sterile zip-lock bag.
    d. Place the infusion bag in a specially designed centrifuge bucket insert (see Figure 9).
      Figure 9
    e. Arrange the insert and the supernatant bag inside the centrifuge bucket with the supernatant bag placed between the insert and the inner wall of the centrifuge bucket (see Figure 10).
      Figure 10
    f. Check that all clamps are closed.
    g. Tape the tubing so that it remains inside the centrifuge bucket during centrifugation (see Figure 11).
      Figure 11
    h. Balance the centrifuge buckets.
    i. Pellet the cells via centrifugation at 880 G for 20 minutes at 2-8°C.
      NOTE: In centrifuges with rotor radius equal to 25 cm, a speed of 1800 RPM is equivalent to 880 G.
  2 Removal of the Supernatant
    a. Remove the infusion bag attached to the supernatant bag, from the centrifuge bucket.
    b. Place the centrifuged infusion bag in the plasma expressor and the attached supernatant bag inside a Plexiglass or equivalent tray on the scale (see Figure 12).
      Figure 12
    c. Tare the scale.
    d. Open the tubing clamp between the two bags.
    e. Transfer most of the supernatant to the supernatant bag after leaving a volume of product appropriate for the patient's weight as determined by the transplant team (see Section II.1.i), taking into account the volume of product that will be recovered in step 3.i below.
    f. Be sure that the cell pellet is not disrupted during transfer of the supernatant.
    g. Empty the tubing between the bags by transferring the air from the supernatant bag to the infusion bag.
    h. Clamp the tubing to the infusion bag and remove the supernatant bag from the scale.
    i. Place the infusion bag on the scale.
    j. Record the displayed weight.
    k. Heat seal the tubing connecting the infusion bag and the supernatant bag, then detach the supernatant bag.
      NOTE: Make sure roller clamp remains attached to the supernatant bag (see Figure 1) as this will be needed for step 3.e of the Recovery of Remaining Cells procedure.
    l. Gently mix the cellular contents of the infusion bag. Keep the infusion bag in the ice mat when completing subsequent steps.
      NOTE: The cell suspension after the completion of this step will be referred to as cell suspension #1.
    m. Remove a 0.2 mL sample of cell suspension #1 for cell count and cell viability tests using sterile technique in the biological safety cabinet. Vortex the sample at the lowest speed for 3-5 seconds.
    n. Perform the cell count and cell viability.
  3 Recovery of Remaining Cells
    NOTE: Follow specific internal protocol of individual transplant center if the transplant center wants to refreeze the remaining cells.
    a. Place the supernatant bag inside a sterile zip-lock bag and then inside the centrifuge insert.
    b. Place the centrifuge insert and the bags in the centrifuge bucket.
    c. Balance the buckets.
    d. Pellet the cells at 880 G for 20 minutes at 2-8°C.
    e. Close roller clamp on supernatant bag before sterile welding.
    f. Sterile weld the supernatant bag to a 150 or 300 mL transfer bag.
    g. Place the supernatant bag containing the pelleted cells which is now attached to the transfer bag on the plasma expressor.
    h. Open the roller clamp between the supernatant bag and the transfer bag.
    i. Express the supernatant from the supernatant bag into the transfer bag without disrupting the pellet, leaving a volume appropriate to add to the infusion bag that will not to exceed the final volume requested by transplant team (See Section II.1.i and step 2.e above).
    j. Gently mix cellular content of the supernatant bag after expression of supernatant and then draw the contents into a 20 or 30 mL syringe using the supernatant sample port (see Figure 2).
      NOTE: The cell suspension after the completion of this step will be referred to as cell suspension #2.
    k. Measure the volume in the syringe.
    l. Transfer 0.2 mL sample of cell suspension #2 from the syringe into a 5 mL test tube for a cell count using sterile technique in the biological safety cabinet. Vortex the sample at the lowest speed for 3-5 seconds.
    m. Perform the cell count.
    n. Inject cell suspension #2 into the product sample port (in Figure 2) on the tubing attached to the infusion bag containing cell suspension #1 to combine the two cell suspensions.
    o. Determine the combined volume and/or weight of the final product.
    p. Proceed to the next section for transplantation preparation steps.
VI PREPARATION OF DUCORD FOR TRANSPLANTATION
  1 BAG Method for Adult Recipients
    a. Remove a 0.9 mL sample for QC testing from the product sample port (see Figure 2) on the tubing attached to the infusion bag using sterile technique with a sterile needle and syringe in a biological safety cabinet. Vortex sample at the lowest speed for 3-5 seconds. This QC sample is used to perform viability and a total nucleated cell count and other testing as recommend (see section VII of the procedure for QUALITY CONTROL TESTS).
    b. Calculate viable cell recovery using the following formula:
      Total Viable Nucleated Cells on the Infusion Ready Product
      Total Viable Nucleated Cells of Cryopreserved Unit Provided on Feedback Sheet
    c. Record all values on the designated laboratory thawing form.
    d. Label the infusion bag with patient and donor information per institutional standard operation procedures (e.g. Demand 128 or equivalent).
    e. Attach a tie tag containing the recipient and donor demographic information to the infusion bag.
    f. Prepare a saline wash bag per physician order by transferring 20-100 mL of 0.9% Sodium Chloride solution into a 150 mL transfer bag with extension tubing. This saline solution will be used to wash the infusion bag after the product is infused into the patient.
    g. Sterile weld the infusion bag to the saline wash bag (see Figure 13). Clamp the tubing between the infusion bag and the saline wash bag, using the clamp on the tubing connected to the infusion bag, on the side closer to the infusion bag.
      Figure 13
    h. Complete appropriate laboratory forms to document the thawing process and final volumes.
    i. Confirm and document, with a second technologist or designee, the ISBT or equivalent barcode affixed and tie tag attached on bag of cells to be transplanted.
    j. Transport product to the site of administration to the patient in a validated transport container at 4-8°C.
    k. Infuse within four hours of thawing.
    l. Infuse the product through a 100 mL burette hemoset 170-260 micron filter at the bedside. Do not use leukoreduction filters
      .
  2 SYRINGE Method for Pediatric Recipients or Recipients on Fluid Restrictions
    a. Place an ISBT barcode label on a 60 mL and 3 mL syringe.
    b. Remove 100 mL burette hemoset 170-260 micron filter set from its packaging.
    c. Clamp the roller clamp on the hemoset tubing.
    d. Spike the 100 mL burette hemoset 170-260 micron filter set into the port on the infusion bag.
    e. Attach a 3-way stopcock to the end of the 100 mL burette hemoset filter line. The stopcock will accommodate a 3 mL syringe (for QC tests) and 60 mL syringe (see Figure 14).
      Figure 14
    f. Mix and pull the cellular product into the 60 mL syringe so the entire volume can be accurately measured.
    g. Attach the 3 mL syringe to the open port on the stopcock.
    h. Adjust the stopcock and use the 3 mL syringe to remove a 0.9 mL sample of product to be used for QC testing. This QC sample is used to perform viability and a total nucleated cell count. Refer to section VII of the procedure for QUALITY CONTROL TESTS.
    i. Detach the 60 mL syringe containing the cellular product and attach it to the lipid compatible 3-way stopcock clamp, the neutral displacement needleless, connector, and the 60 inch, 2.4 mL extension set tubing (see Figure 15).
      Figure 15
    j. Prime the extension set tubing with cellular product (2.4 mL capacity). Be sure to place the stopcock in the OFF position after the tubing has been primed.
    k. Attach rubber shod clamp to the tubing to ensure there is no leakage.
    l. Calculate viable cell recovery using the following formula:
      Total Viable Nucleated Cells on the Infusion Ready Product
      Total Viable Nucleated Cells of Cryopreserved Unit Provided on Feedback Sheet
    m. Record all values on the laboratory thawing form.
    n. Label the syringe with patient and donor information per institutional standard operation procedures (Demand 128 or equivalent).
    o. Attach a tie tag containing the recipient and donor demographic information to the syringe.
    p. Complete appropriate laboratory paperwork to record all steps in the procedure and volumes recovered.
    q. Confirm with a second technologist or designee that the affixed label on the syringe and tie tag attached to the syringe barrel match. Document that this step was completed on transplant center form.
    r. Transport product to the site of administration in a validated transport container at 4-8°C.
    s. Infuse within four hours of thawing.
    t. Do not use leukoreduction filters.
VII QUALITY CONTROL TESTS
  The following tests are recommended.
  1. Cell Counts: perform on final product to be infused, diluted product (optional), cell suspension #1, cell suspension #2, combined cell suspension (#1 and #2) and cells for freezing from the supernatant bag if requested by the transplant center.
  2. Viability test by Trypan Blue: perform on initial cell product after first centrifugation and on the final product.
  3. Colony assay for CFU-GM, GEMM and BFU-E: perform on final product to be infused.
  4. Viable CD34^+ determination by flow analysis: perform on final product to be infused.
  5. Sterility Test: perform on 10 mL of supernatant from the final wash (5 mL for aerobic and 5 mL for anaerobic cultures).
  6. RFLP or equivalent DNA-based identity test: perform on approximately 1 × 10^6 cells (0.2 mL) from infusion-ready product, upon request.
VIII EMERGENCY PRODUCT RECOVERY IN THE EVENT OF A CONTAINER FAILURE
  1. Handle the cryobag with extreme caution when removing it from the liquid nitrogen, metal cassette and the protective overwrap. Cryobags can be very fragile. This is applicable both during inspection of the product upon arrival and during the thawing process.
  2. Wipe the external surface of the cryobag with isopropyl alcohol before the cryobag is placed inside a sterile zip-lock bag. This process positions the thawing laboratory to 30 of 30 potentially recover the product in the case of an unexpected leak or container failure during thawing or centrifugation.
  3. Contact the CCBB Laboratory Supervisor at 919-257-9273 or 919-668-2066 if, during thawing, any portion of the product or container appears to be damaged or compromised. The CCBB will provide advice to determine the best way to recovery the product from the compromised container. The CCBB will also provide further instruction for return of the container, if requested, and a prompt investigation will follow. The transplant physician and the local laboratory director should also be notified immediately.
  4. If the bag is compromised, move further handling into biological safety cabinet after thawing.
  5. It is the transplant physician's (or designee's) responsibility to determine whether the product will be used or discarded if the container is compromised at any step of the procedure.
  6. If the transplant physician (or designee) decides that the product should be used, recovery of the product may be attempted as described below.
    a. Use a long (3-5 inch) blunt needle (a sterile spinal needle with trochar removed if available).
    b. Attach the blunt needle to a sterile 60 mL syringe.
    c. Aspirate the product and inject into a sterile transfer bag.
      NOTE: More than one syringe may be needed if the volume in the bag exceeds 60mL at the time of violation of the integrity of the bag.
    d. Complete processing of the transferred product as indicated.
    e. Perform sterility test on the product sample after final processing.
      NOTE: Alert the clinical team at the transplant center that the product was violated and could potentially be contaminated.
  7. Save the ruptured bag if possible. When contacted about the container failure, the CCBB Laboratory Supervisor will provide further instructions for return of the container, if requested. A prompt CCBB investigation will follow, as applicable.

Distributed by:
Duke University School of Medicine
Carolinas Cord Blood Bank
North Pavilion Building, Suite 1400
2400 Pratt Street
Durham, NC 27705
U.S. License #1870

PACKAGE LABEL

PRINCIPAL DISPLAY PANEL - Double Compartment Cryobag (80-20) Label

See
Attached
Documents

Product:
S1333000

Volume:
25 mL

Store at
− 150°C
or colder

Cryopreserved,
HPC, Cord Blood
Duke University School of Medicine
Carolinas Cord Blood Bank Durham NC

PRINCIPAL DISPLAY PANEL - Canister Label

PRINCIPAL DISPLAY PANEL - Tie Tag Label

CRYOPRESERVED
HPC, CORD BLOOD

25 mL